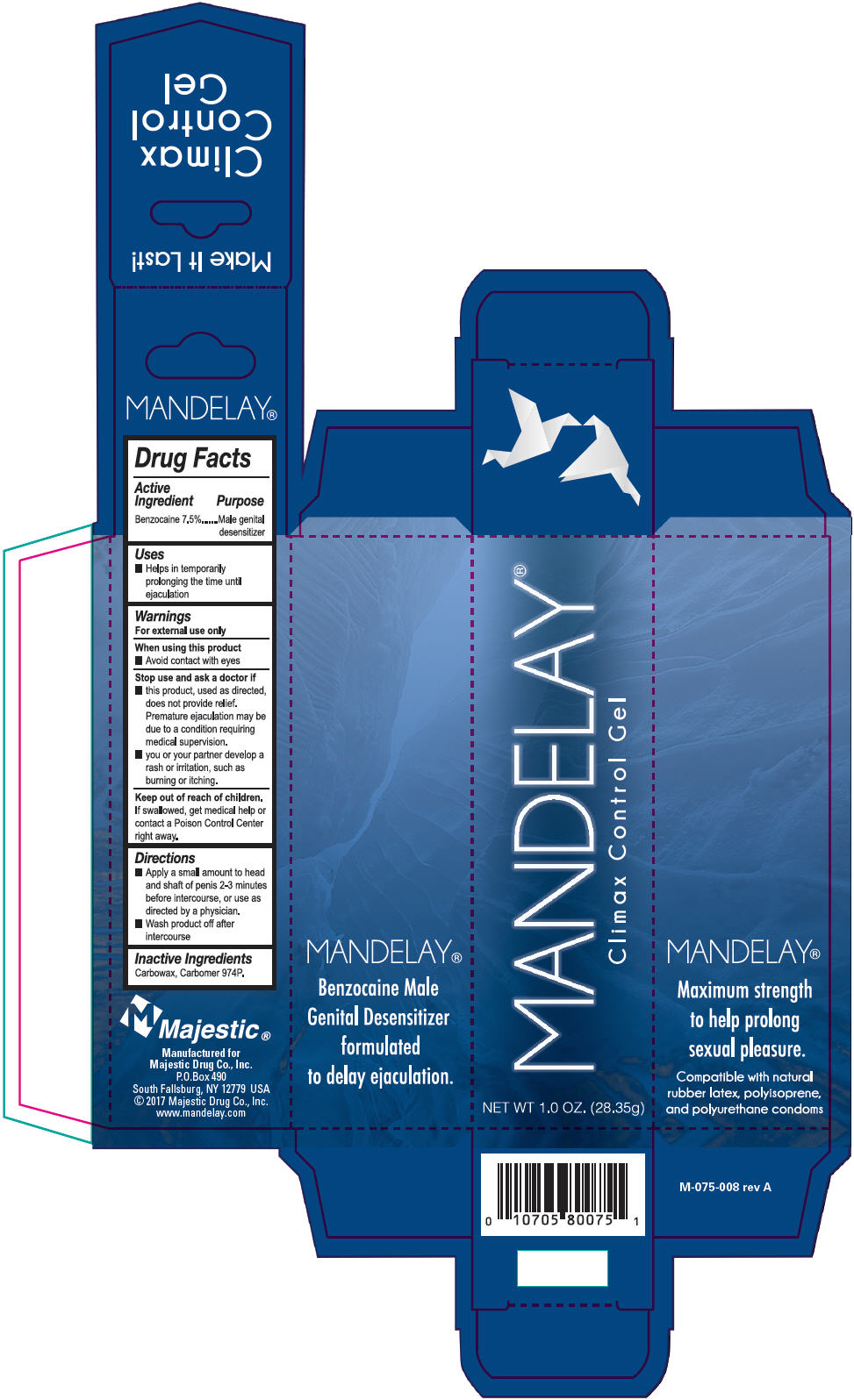 DRUG LABEL: Mandelay 
NDC: 10705-077 | Form: GEL
Manufacturer: Majestic Drug Co., INC.
Category: otc | Type: HUMAN OTC DRUG LABEL
Date: 20171109

ACTIVE INGREDIENTS: Benzocaine 2.13 g/28.35 g
INACTIVE INGREDIENTS: Carbomer Homopolymer Type B (Allyl Pentaerythritol Crosslinked)

MANDELAY®

Drug Facts

Active Ingredient

Benzocaine 7.5%

Purpose

Male genital desensitizer

Uses

- Helps in temporarily prolonging the time until ejaculation

Warnings

For external use only

When using this product

- Avoid contact with eyes

Stop use and ask a doctor if

- this product, used as directed,does not provide relief. Premature ejaculation may be due to condition requiring medical supervision.
- you or your partner develop a rash or irritation, such as burning or itching.

Keep out of reach of children. If swallowed, get medical help or contact a Poison Control Center right away.

Directions

- Apply a small amount to head and shaft of penis 2-3 minutes before intercourse, or use as directed by a physician.
- Wash product off after intercourse.

Inactive Ingredients

Carbowax, Carbomer 974P.

PRINCIPAL DISPLAY PANEL - 28.35 g Tube Box

MANDELAY®

Climax Control Gel

NET WT 1.0 OZ. (28.35g)